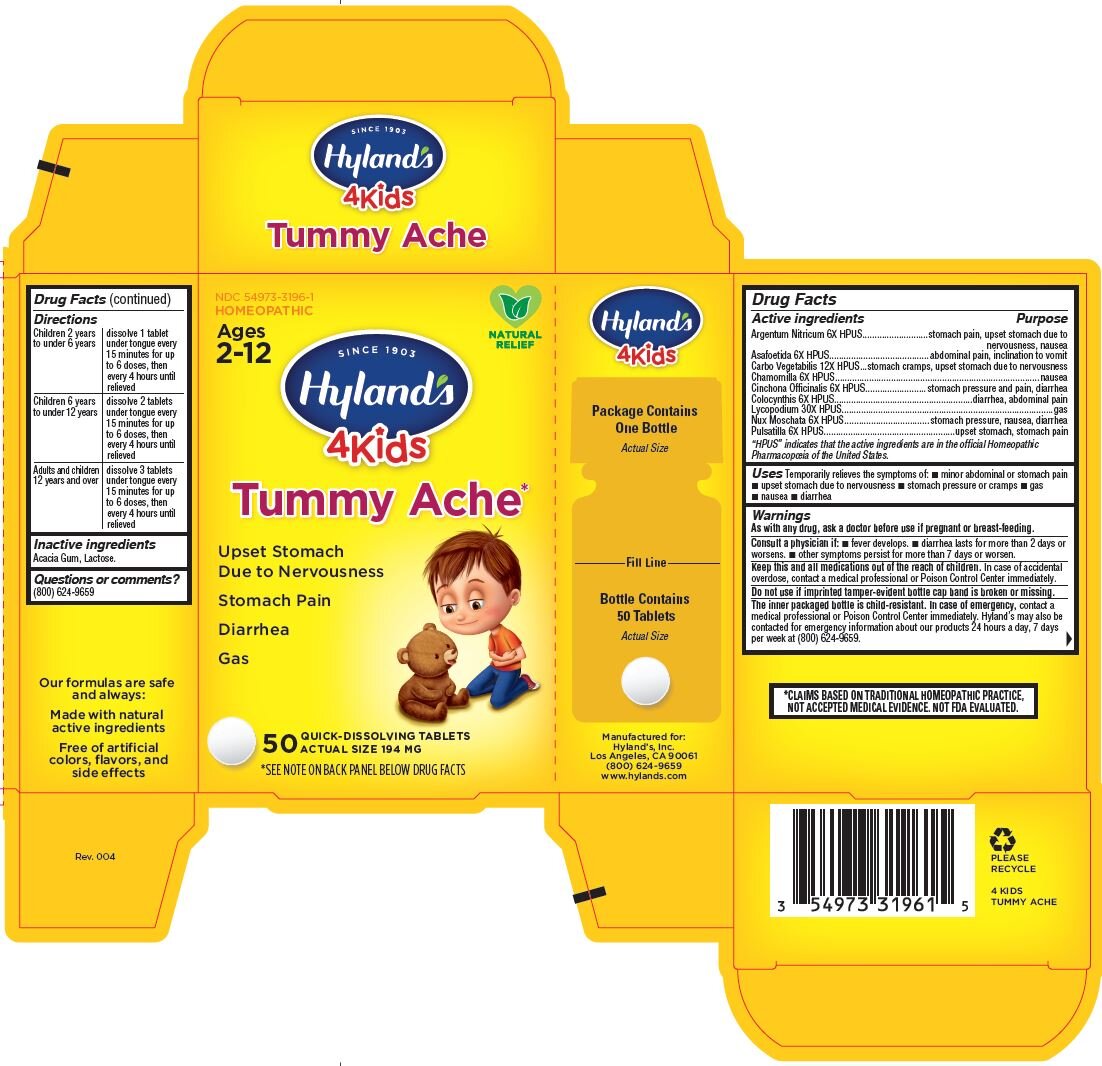 DRUG LABEL: Tummy Ache 4Kids
NDC: 54973-3196 | Form: TABLET
Manufacturer: Hyland's Inc.
Category: homeopathic | Type: HUMAN OTC DRUG LABEL
Date: 20221214

ACTIVE INGREDIENTS: SILVER NITRATE 6 [hp_X]/1 1; ASAFETIDA 6 [hp_X]/1 1; ACTIVATED CHARCOAL 12 [hp_X]/1 1; MATRICARIA RECUTITA 6 [hp_X]/1 1; CINCHONA OFFICINALIS BARK 6 [hp_X]/1 1; CITRULLUS COLOCYNTHIS FRUIT PULP 6 [hp_X]/1 1; LYCOPODIUM CLAVATUM SPORE 30 [hp_X]/1 1; NUTMEG 6 [hp_X]/1 1; PULSATILLA VULGARIS 6 [hp_X]/1 1
INACTIVE INGREDIENTS: ACACIA; LACTOSE

Hyland's 4Kids Tummy Ache

Drug Facts

Active ingredients

Active ingredients | Purpose
Argentum Nitricum 6X HPUS | stomach pain, upset stomach due to nervousness, nausea
Asafoetida 6X HPUS | abdominal pain, inclination to vomit
Carbo Vegetabilis 12X HPUS | stomach cramps, upset stomach due to nervousness
Chamomilla 6X HPUS | nausea
Cinchona Officinalis 6X HPUS | stomach pressure and pain, diarrhea
Colocynthis 6X HPUS | diarrhea, abdominal pain
Lycopodium 30X HPUS | gas
Nux Moschata 6X HPUS | stomach pressure, nausea, diarrhea
Pulsatilla 6X HPUS | upset stomach, stomach pain

"HPUS" indicates the active ingredients are in the official Homeopathic Pharmacopœia of the United States.

Uses

Temporarily relieves the symptoms of: • minor abdominal or stomach pain • upset stomach due to nervousness • stomach pressure or cramps • gas • nausea • diarrhe

Warnings

PREGNANCY OR BREAST FEEDING

As with any drug, ask a doctor before use if pregnant or breast-feeding.

ASK DOCTOR

Consult a physician if:

- fever develops
- diarrhea lasts for more than 2 days worsens
- other symptoms persist for more than 7 days or worsen

KEEP OUT OF REACH OF CHILDREN

Keep this and all medications out of the reach of children. In case of accidental overdose, contact a medical professional or Poison Control Center immediately.

Do not use if imprinted tamper-evident bottle cap band is broken or missing.

The inner packaged bottle is child-resistant. In case of emergency, contact a medical professional or Poison Control Center immediately. Hyland’s may also be contacted for emergency information about our products 24 hours a day, 7 days per week at (800) 624-9659.

*CLAIMS BASED ON TRADITIONAL HOMEOPATHIC PRACTICE, NOT ACCEPTED MEDICAL EVIDENCE. NOT FDA EVALUATED.

Drug Facts (continued)

Directions

children 2 years to under 6 years | dissolve 1 tablet under tongue every 15 minutes for up to 6 doses until relieved; then every 4 hours as required
children 6 years to under 12 years | dissolve 2 tablets under tongue every 15 minutes for up to 6 doses until relieved; then every 4 hours as required
adults and children 12 years and over | dissolve 3 tablets under tongue every 15 minutes for up to 6 doses until relieved; then every 4 hours as required

Inactive ingredients

Acacia Gum, Lactose.

Questions or comments?

(800) 624-9659

PURPOSE

Temporarily relieves minor abdominal and stomach pain, upset stomach due to nervousness, stomach pressure and cramps, gas, nausea, and diarrhea.

PRINCIPAL DISPLAY PANEL - 50 Tablet Bottle Carton

NDC 54973-3196-1
HOMEOPATHIC

Natural
Relief

Ages
2-12

SINCE 1903
Hyland's
4Kids

Tummy Ache*

Upset Stomach
Due to Nervousness

Stomach Pain

Diarrhea

Gas

50 QUICK-DISSOLVING TABLETS
ACTUAL SIZE 194 MG

*SEE NOTE ON BACK PANEL BELOW DRUG FACTS